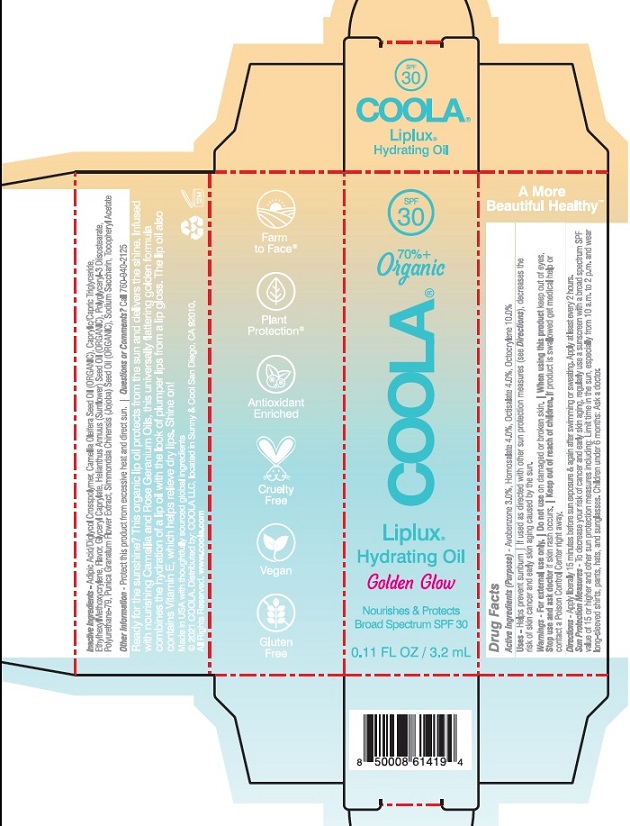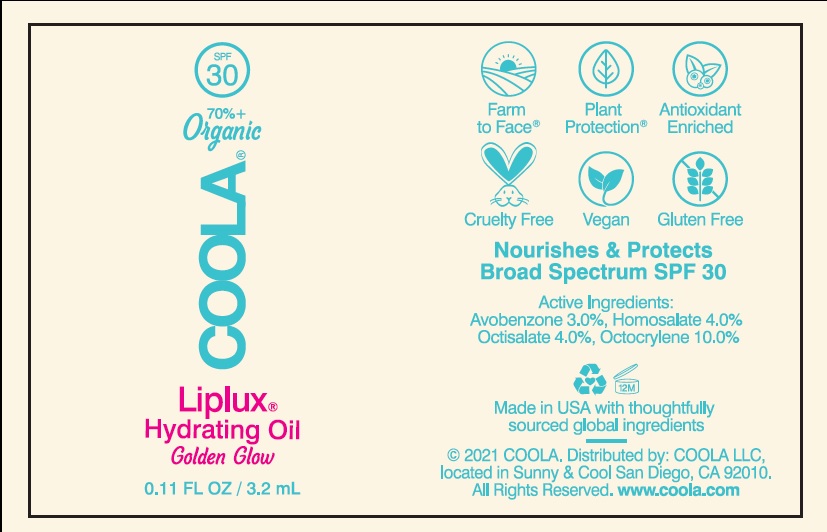 DRUG LABEL: COOLA Liplux Hydrating Oil SPF 30
NDC: 79753-018 | Form: OIL
Manufacturer: COOLA LLC
Category: otc | Type: HUMAN OTC DRUG LABEL
Date: 20231220

ACTIVE INGREDIENTS: AVOBENZONE 3.0 g/100 mL; HOMOSALATE 4.0 g/100 mL; OCTISALATE 4.0 g/100 mL; OCTOCRYLENE 10.0 g/100 mL
INACTIVE INGREDIENTS: ADIPIC ACID/DIGLYCOL CROSSPOLYMER (20000 MPA.S); CAMELLIA OIL; CAPRYLIC/CAPRIC/LAURIC TRIGLYCERIDE; ETHYLHEXYL METHOXYCRYLENE; GLYCERYL CAPRYLATE; SUNFLOWER OIL; POLYGLYCERYL-3 DIISOSTEARATE; MEDIUM-CHAIN TRIGLYCERIDES; PUNICA GRANATUM FLOWER; JOJOBA OIL; SACCHARIN SODIUM; .ALPHA.-TOCOPHEROL ACETATE

COOLA Liplux Hydrating Oil SPF 30

Drug Facts

Active Ingredients

Avobenzone 3.0%, Homosalate 4.0%, Octisalate 4.0%, Octocrylene 10.0%

Purpose

Suncreen

Uses

- helps prevent sunburn

- if used as directed with other sun protection measures

(see Directions), decreases the risk of skin cancer and

early skin aging caused by the sun

Warnings

For external use only

Do not use on damaged or broken skin

When using this product keep out of eyes.

Stop use and ask doctor if skin rash occurs

Keep out of reach of children. If product is swallowed, get

medical help or contact a Poison Control Center right away.

DOSAGE AND ADMINISTRATION

Directions - Apply liberally 15 minutes before sun exposure & again after swimming or sweating. Apply at least every 2 hours.
Sun Protection Measures - To decrease your risk of cancer and early skin aging. Regularly use a sunscreen with a broad
spectrum SPF of 15 or higher and other sun protection
measures including: limit time in the sun, especially from: 10 a.m. - 2 p.m. and wear
long-sleeve shirts, pants, hats, and sunglasses. Children under 6 months: Ask a doctor

INACTIVE INGREDIENT

Inactive Ingredients-Adipic Acid/Diglycol Crosspolymer,Camellia Oleifera Seed Oil (ORGANIC),Caprylic/Capric Triglyceride,Ethylhexylmethoxycrylene,Flavor,Glyceryl Caprylate,Helianthus Annus (Sunflower) Seed Oil (ORGANIC),Polyglyceryl-3 Diisostearate,Polyurethane-79,Punica Granatum Flower Extract,Simmondsia Chinensis (Jojoba) Seed Oil (ORGANIC),Sodium Saccharin,Tocopheryl Acetate

Other information

- protect this product from excessive heat and direct sun

Questions or comments?
Call 760-940-2125

COOLA Label

SPF

30

70%+

Organic

COOLA®

Liplux®

Hydrating Oil

Golden Glow

Nourishes & Protects

Broad Spectrum SPF 30

0.11 FL OZ / 3.2 mL

©2021 COOLA. Distributed by: COOLA LLC, located in

Sunny & Cool San Diego, CA 92010.

Carton

Bottle

res